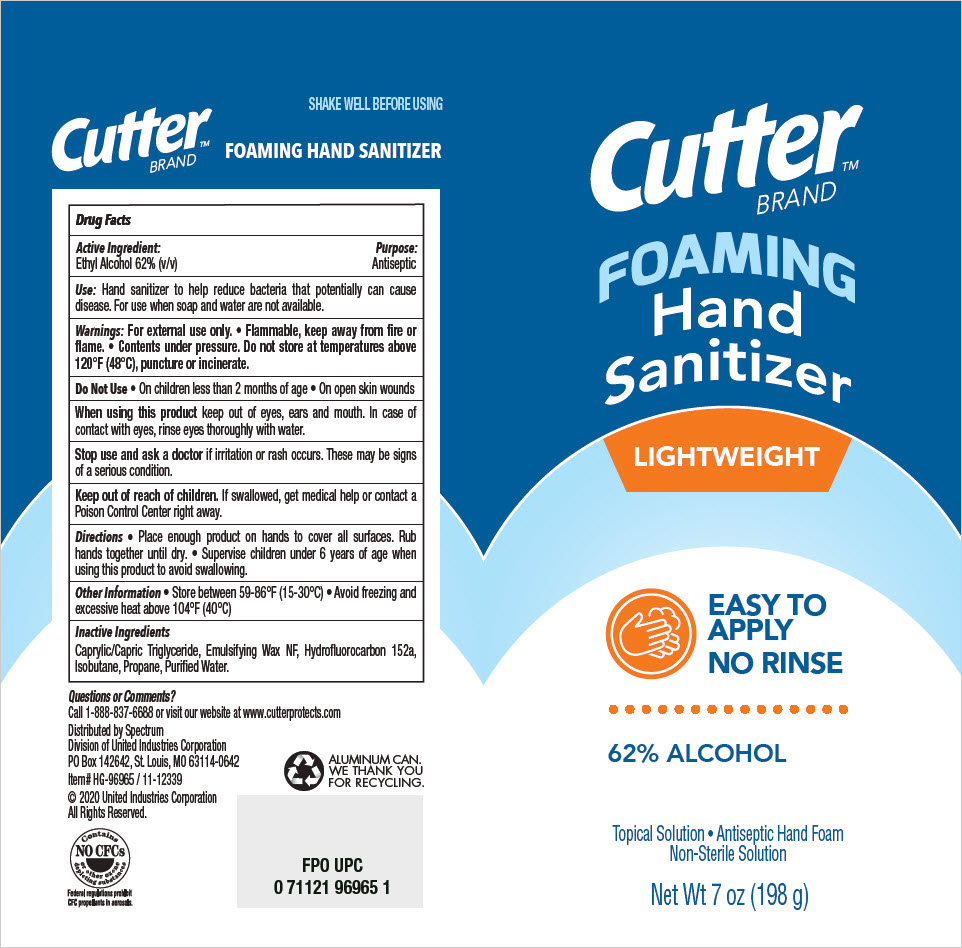 DRUG LABEL: Cutter Brand Foaming Hand Sanitizer
NDC: 79364-1681 | Form: AEROSOL, FOAM
Manufacturer: United Industries Corporation
Category: otc | Type: HUMAN OTC DRUG LABEL
Date: 20200810

ACTIVE INGREDIENTS: Alcohol 0.51395 g/1 g
INACTIVE INGREDIENTS: MEDIUM-CHAIN TRIGLYCERIDES; 1,1-DIFLUOROETHANE; Isobutane; Propane; Water

Cutter™ Brand Foaming Hand Sanitizer

Drug Facts

Active Ingredient

Ethyl Alcohol 62% (v/v)

Purpose

Antiseptic

Use

Hand sanitizer to help reduce bacteria that potentially can cause disease. For use when soap and water are not available.

Warnings

For external use only.

- Flammable, keep away from fire or flame.
- Contents under pressure. Do not store at temperatures above 120°F (48°C), puncture or incinerate.

Do Not Use

- On children less than 2 months of age
- On open skin wounds

When using this product keep out of eyes, ears and mouth. In case of contact with eyes, rinse eyes thoroughly with water.

Stop use and ask a doctor if irritation or rash occurs. These may be signs of a serious condition.

Keep out of reach of children. If swallowed, get medical help or contact a Poison Control Center right away.

Directions

- Place enough product on hands to cover all surfaces. Rub hands together until dry.
- Supervise children under 6 years of age when using this product to avoid swallowing.

Other Information

- Store between 59-86°F (15-30°C)
- Avoid freezing and excessive heat above 104°F (40°C)

Inactive Ingredients

Caprylic/Capric Triglyceride, Emulsifying Wax NF, Hydrofluorocarbon 152a, Isobutane, Propane, Purified Water.

Questions or Comments?

Call 1-888-837-6688 or visit our website at www.cutterprotects.com

Distributed by Spectrum
Division of United Industries Corporation
PO Box 142642, St. Louis, MO 63114-0642

PRINCIPAL DISPLAY PANEL - 198 g Can Label

Cutter™
BRAND

FOAMING
Hand
Sanitizer

LIGHTWEIGHT

EASY TO
APPLY
NO RINSE

62% ALCOHOL

Topical Solution • Antiseptic Hand Foam
Non-Sterile Solution

Net Wt 7 oz (198 g)